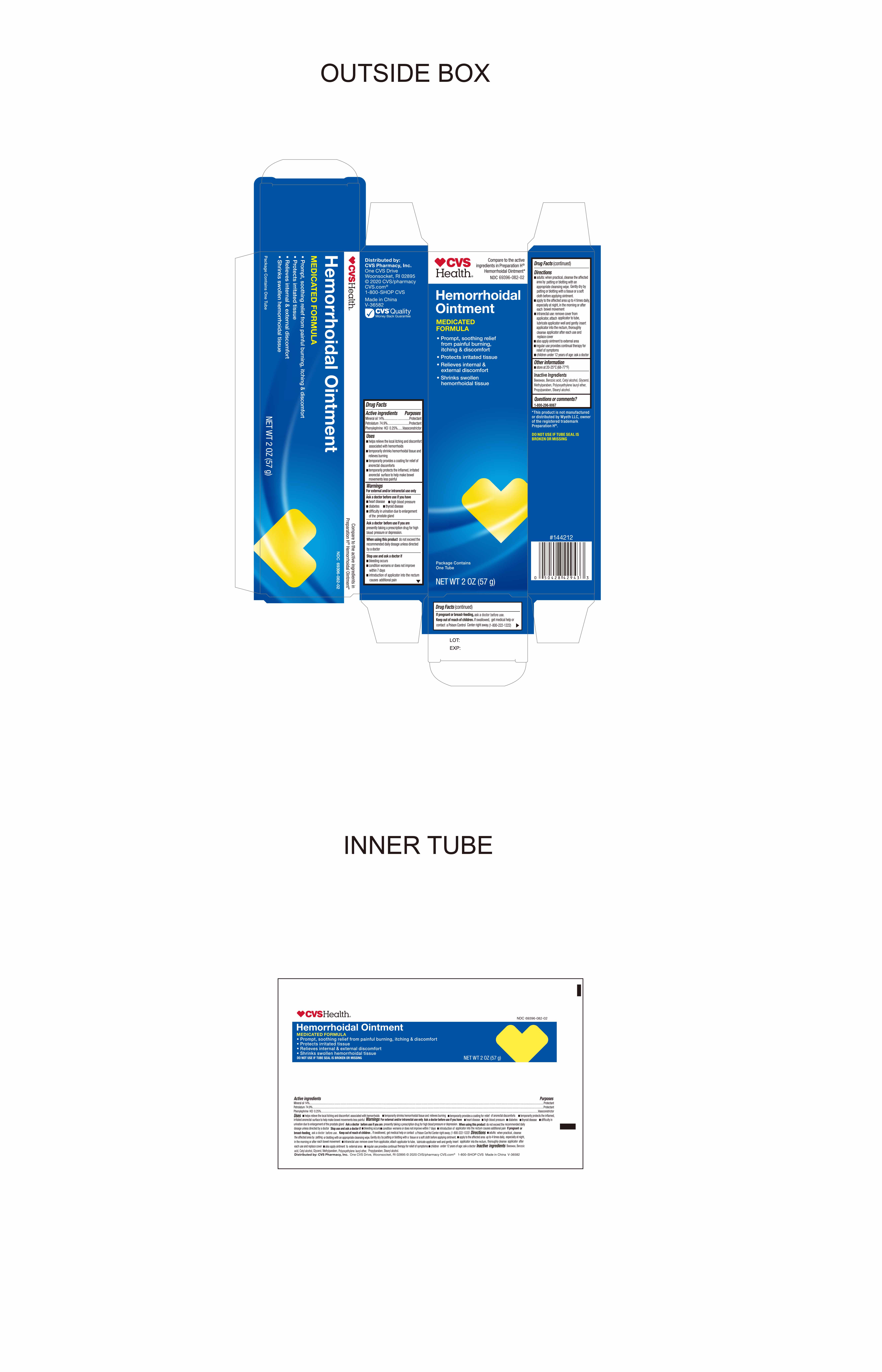 DRUG LABEL: HemorrhoidalOintment
NDC: 69396-082 | Form: OINTMENT
Manufacturer: Trifecta Pharmaceuticals USA LLC
Category: otc | Type: HUMAN OTC DRUG LABEL
Date: 20241218

ACTIVE INGREDIENTS: MINERAL OIL 14 g/100 g; PETROLATUM 74.9 g/100 g; PHENYLEPHRINE HYDROCHLORIDE 0.25 g/100 g
INACTIVE INGREDIENTS: BENZOIC ACID; STEARYL ALCOHOL; CETYL ALCOHOL; LAURETH-23; PROPYLPARABEN; METHYLPARABEN; YELLOW WAX; GLYCERIN

CVS Hemorrhoidal Ointment

Active Ingredient

Phenylephrine HCI 0.25%

Purpose

Vasoconstrictor

Active Ingredient

Mineral Oil 14%

Purpose

Protectant

Active Ingredient

Petrolatum 74.9%

Purpose

Protectant

Uses

- Helps relieve the local itching and discomfort associated with hemorrhoids
- Temporarily shrinks hemorrhoidal tissue and relieves burning
- Temporarily provides a coating for relief of anorectal discomforts
- Temporarily profects the inflamed, irritated anorectal surface to help make bowel movements less painful

Warnings

For external and/or intrarectal use only

Ask doctor before use if you have

- heart disease
- high blood pressure
- thyroid disease
- diabetes
- difficulty urinating due to an enlarged prostate gland

Ask doctor before use if you are presently taking a prescription drug for high blood pressure or depression

Stop Use and Ask Doctor if

- Bleeding occurs
- Condition worsens or does not improve within 7 days
- Introduction of applicator into the rectum causes additional pain

If Pregnant or Breast-Feeding

Ask a doctor before use

Keep out of reach of children

If swallowed get medical help or contact a Poison Control Center right away (1-800-222-1222)

Directions

Adults:

- When practical, cleanse the affected area by patting or blotting with an appropriate cleansing wipe. Gently dry by patting or blotting with a tissue or with a soft cloth before applying ointment
- Apply to the affected area up to 4 times daily, especially at night, in the morning or after each bowel movement
- Intrarectal Use: Remove cover from applicator, attach applicator to tube, lubricate applicator well, and gently insert applicator into rectum. thoroughly cleanse applicator after each use and replace cover.
- Also apply ointment to external area
- Regular use provides continual therapy for relief of symptoms
- Children under 12 years of age: ask a doctor

Other Information

- Store at room temperature 20°-25°C (68°-77°F)

Questions? Call 1-888-296-9067

Distributed By

CVS Pharmacy Inc.

One CVS Drive

Woonsocket, RI 02895

©2020 CVS Pharmacy

CVS.com

1-800-SHOP CVS

Made in China

V-36582

CVS Quality Money Back guarantee

This product is not manufactured or distributed by Wyeth LLC, owner of registered trademark Preparation H®

Inactive Ingredients

Beeswax, Benzoic Acid, Cetyl alcohol, Glycerol, Methylparaben, Polyoxyethylene lauryl ether, Propylparaben, Stearyl alcohol